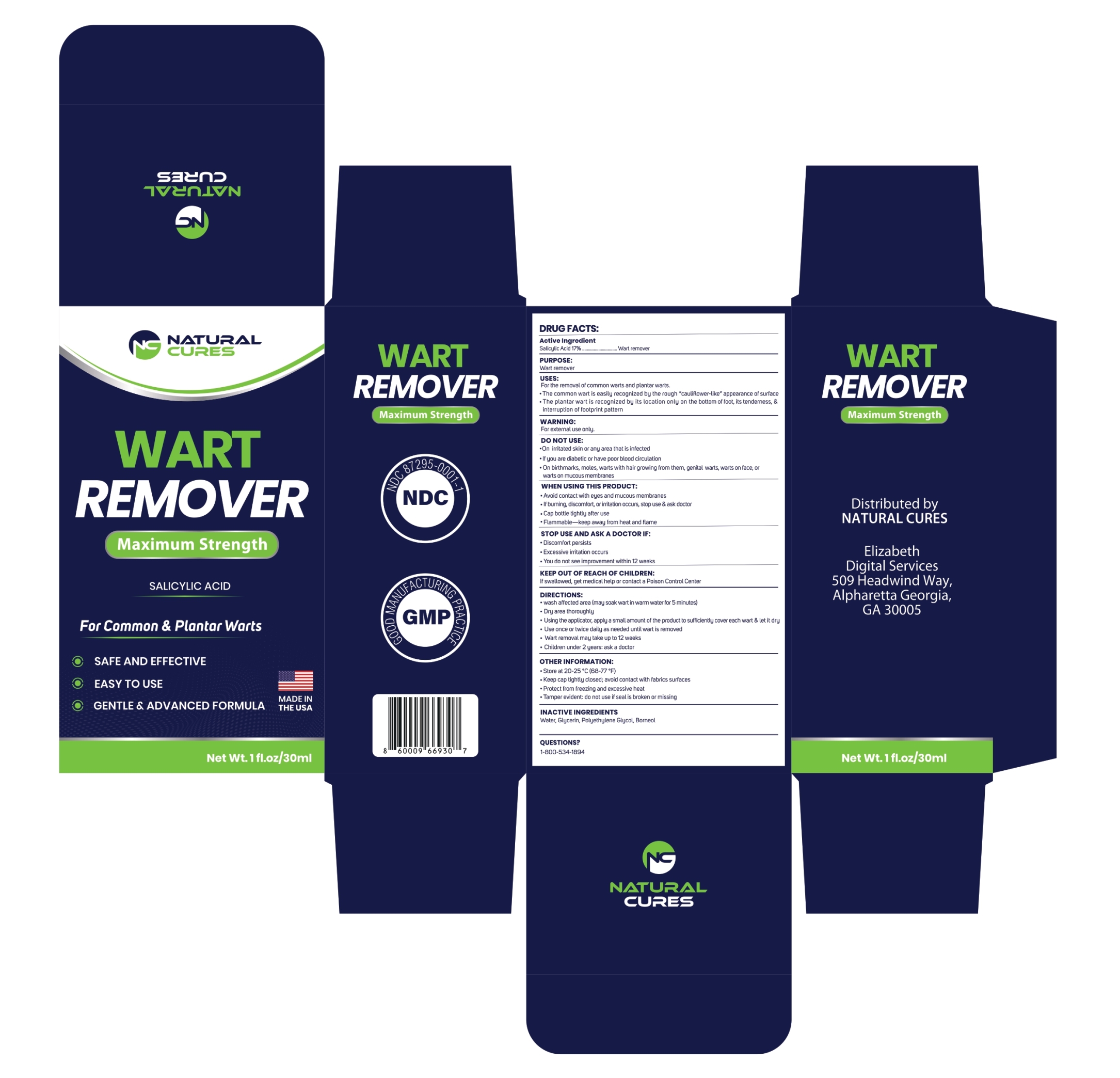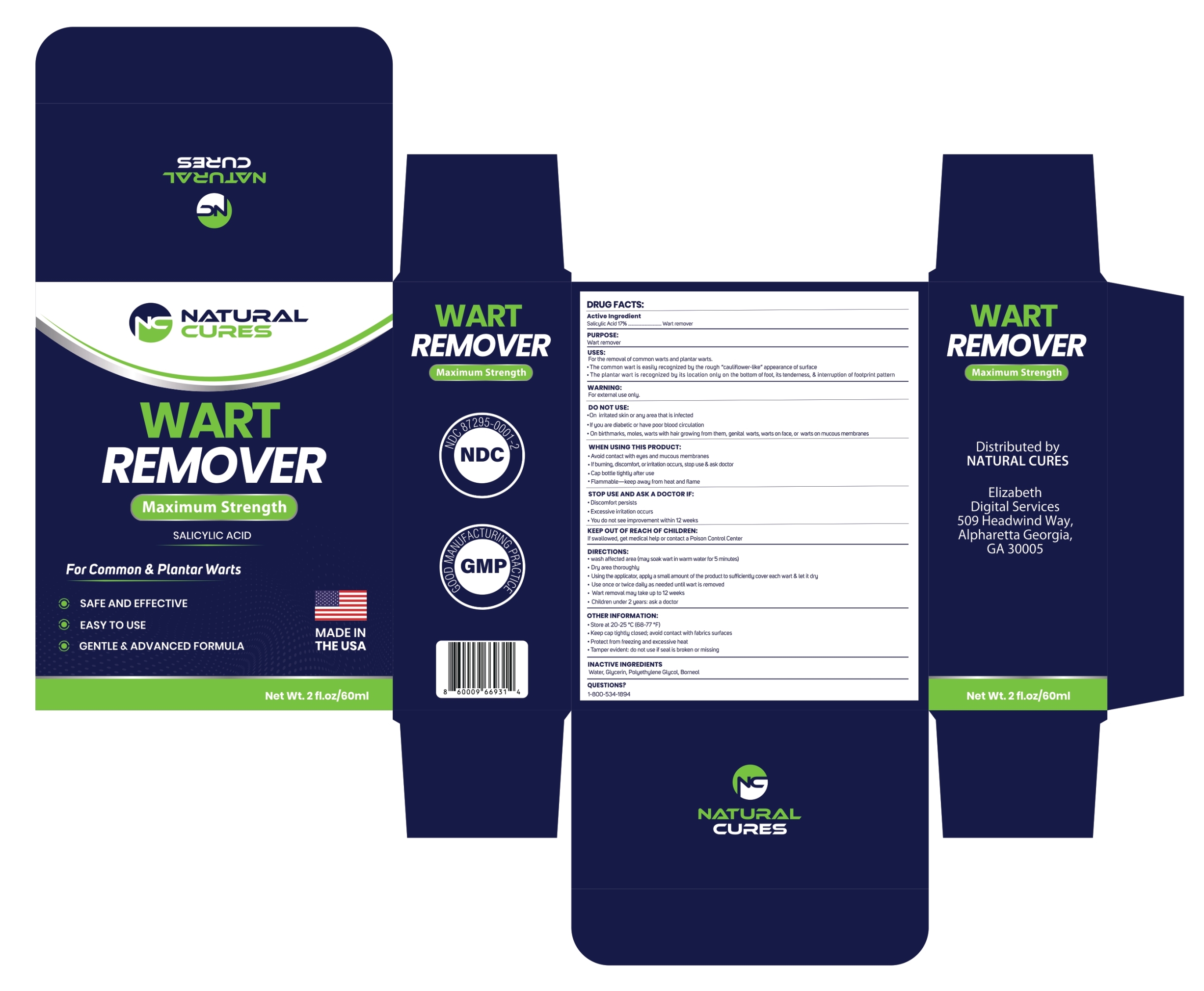 DRUG LABEL: Wart Remover-SALICYLIC ACID
NDC: 87295-0001 | Form: LIQUID
Manufacturer: Ecommerce Digital Sales LLC
Category: otc | Type: HUMAN OTC DRUG LABEL
Date: 20260224

ACTIVE INGREDIENTS: SALICYLIC ACID 17 g/100 mL
INACTIVE INGREDIENTS: WATER; GLYCERIN; POLYETHYLENE GLYCOL, UNSPECIFIED; BORNEOL

Wart Remover Salicylic Acid

Active Ingredient

Salicylic Acid.......17%

PURPOSE:

Wart Remover

USES:

For the removal of common warts and plantar warts.

- The common wart is easily recognized by the rough ''cauliflower-like'' appearance of surface
- The planter wart is recognized by its location only on the bottom of foot, its tenderness, & interruption of footprint pattern

WARNING:

For external use only.

DO NOT USE:

- On irritated skin or any area that is infected
- If you are diabetic or have poor blood circulation
- On birthmarks, moles, warts with hair growing from them, genital warts, warts on face, or warts on mucus membranes

WHEN USING THIS PRODUCT:

- Avoid contact with eyes and mucus membrans
- if burning,discomfort or irritation occurs, stop use & ask a doctor
- Cap bottle tightly after use
- Flammble-keep away from heat and flame

STOP USE AND ASK A DOCTOR IF:

- Discomfort persists
- Excessive irritation occurs
- You do not see improvement within 12 weeks

KEEP OUT OF REACH OF CHILDREN:

If swallowed, get medical help or contact a Poison Control Center

DIRECTIONS

- Wash affected area (may soak wart in warm water for 5 minutes)
- Dry area thoroughly
- Using the applicator, apply a small amount of the product to sufficiently cover each wart & let it dry
- Use once or twice daily as needed until wart is removed
- Wart removal may take upto 12 weeks
- Children under 2 years: ask a doctor

OTHER INFORMATION:

- Store at 20-25 °C (68-77 °F)
- Keep cap tightly closed;avoid contact with fabrics surfaces
- Protect from freezing and excessive heat
- Tamper evident: do not use if seal is broken or missing

INACTIVE INGREDIENT

Water, Gycerin, Polyethylene Glycol, Borneol

QUESTIONS ?

1-800-534-1894